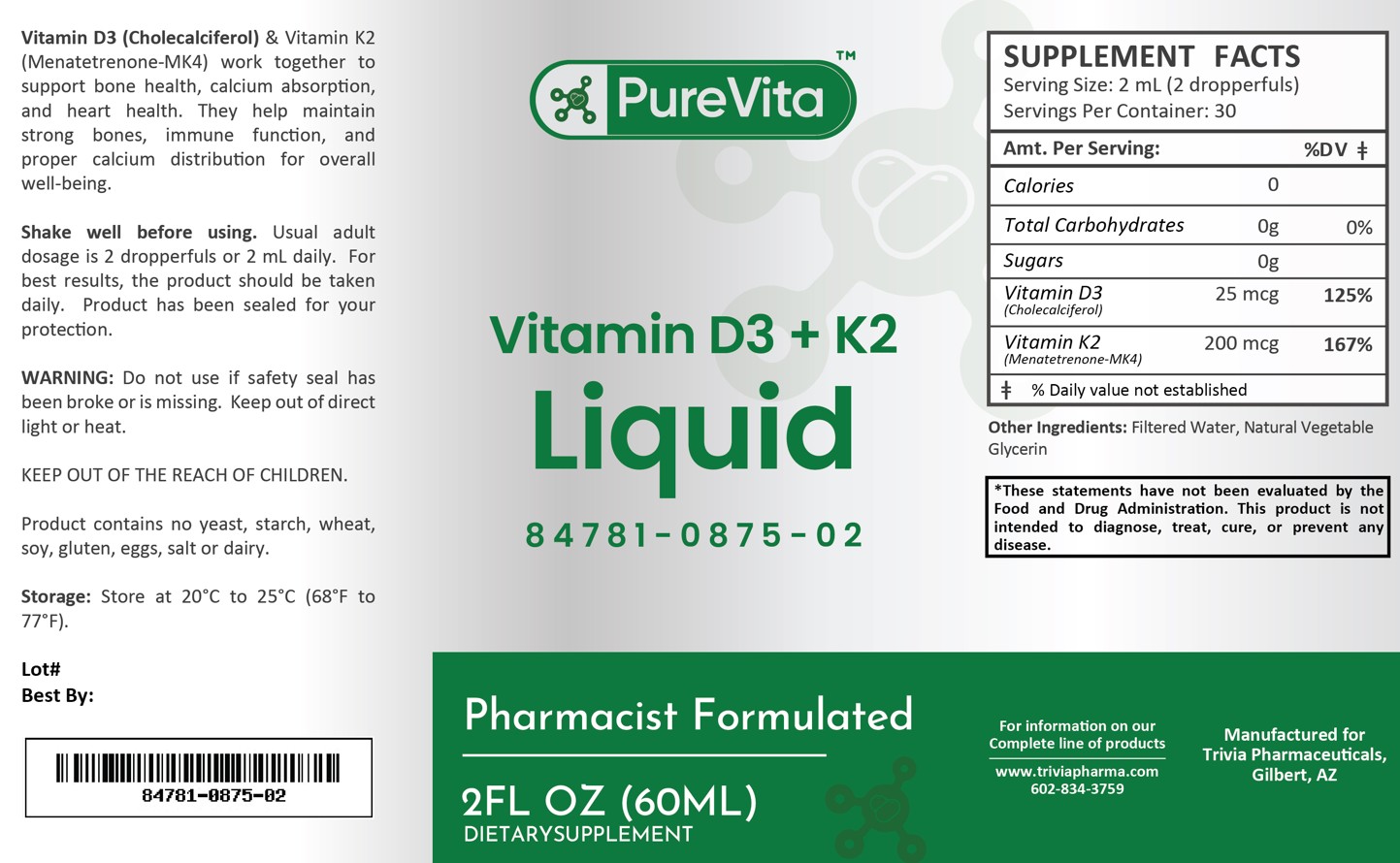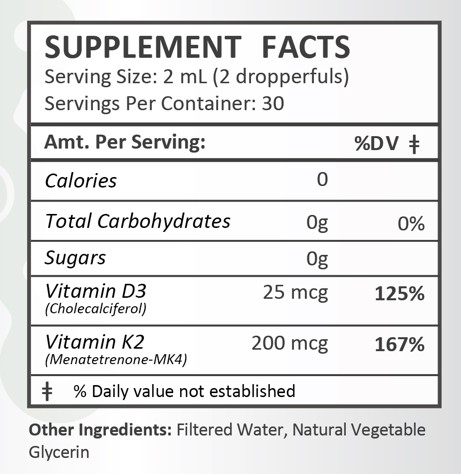 DRUG LABEL: PureVita Vitamin D3/K2
NDC: 84781-875 | Form: LIQUID
Manufacturer: Trivia Pharmaceuticals, LLC
Category: other | Type: Dietary Supplement
Date: 20250311

ACTIVE INGREDIENTS: CHOLECALCIFEROL 25 ug/2 mL; MENATETRENONE 200 ug/2 mL

PureVita Vtiamin D3/K2 Liquid

Health Claim:

PureVita Vitamin D3 + K2 Liquid

Description:

Pure Vita Vitamin D3 (Cholecalciferol) and Vitamin K2 (Menatetrenone-MK4) work together to support bone helath, calcium absorption and heart health. They help maintain strong bones, immune function and proper calcium distribution for overall well-being.

This listed product is not a National Drug Code, but instead has merely been formatted to comply with standard industry practice for pharmacy and insurance computer systems.

Warnings:

Do not use if safety seal has been broken or is missing. Keep out of direct light or heat.

KEEP OUT OF THE REACH OF CHILDREN.

Product contains no yeast, starch, wheat, soy, gluten, eggs, salt or dairy.

Dosage and Administration:

Usual adult dose is 2 dropperfuls or 2 mL daily. For the best results, the product should be taken daily. Product has been sealed for your protection.

How Supplied:

PureVita Vitamin D3 + K2 mg Liquid is supplied as clear, white liquid.

84781-0875-02

Reserved for Professional Recommendation

All prescriptions using this product shall be pursuant to state statutes as applicable. This is not an Orange Book product. There are no implied or explicit claims on therapeutic equivalence.

Manufactured for:
Trivia Pharmaceuticals

Gilbert, AZ

Storage:

Storage: Store at 20oC to 25oC (68oF to 77oF).